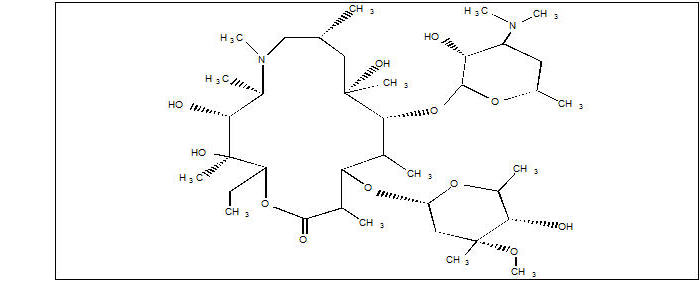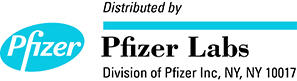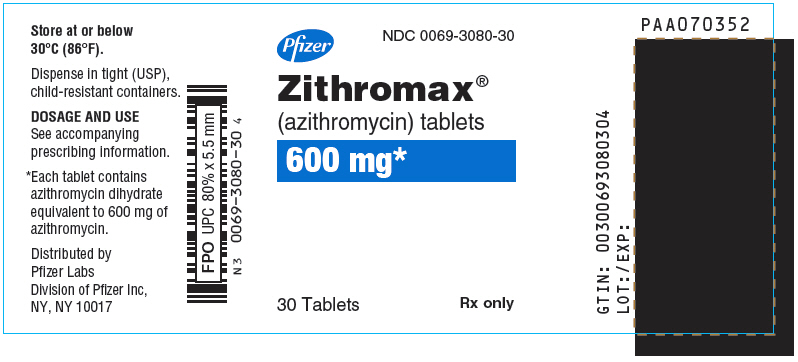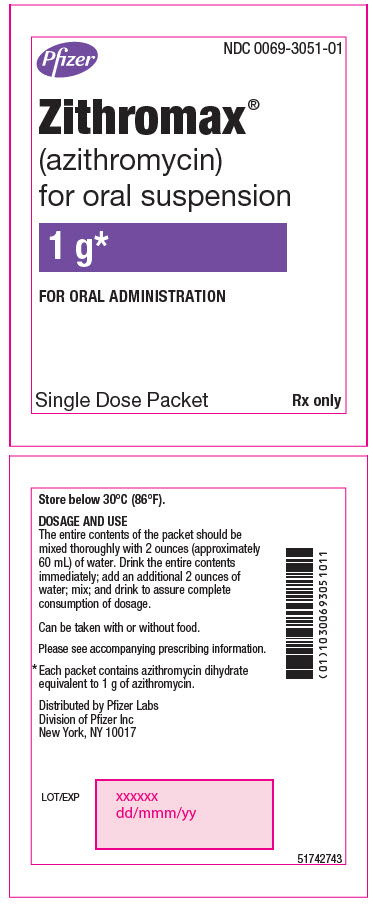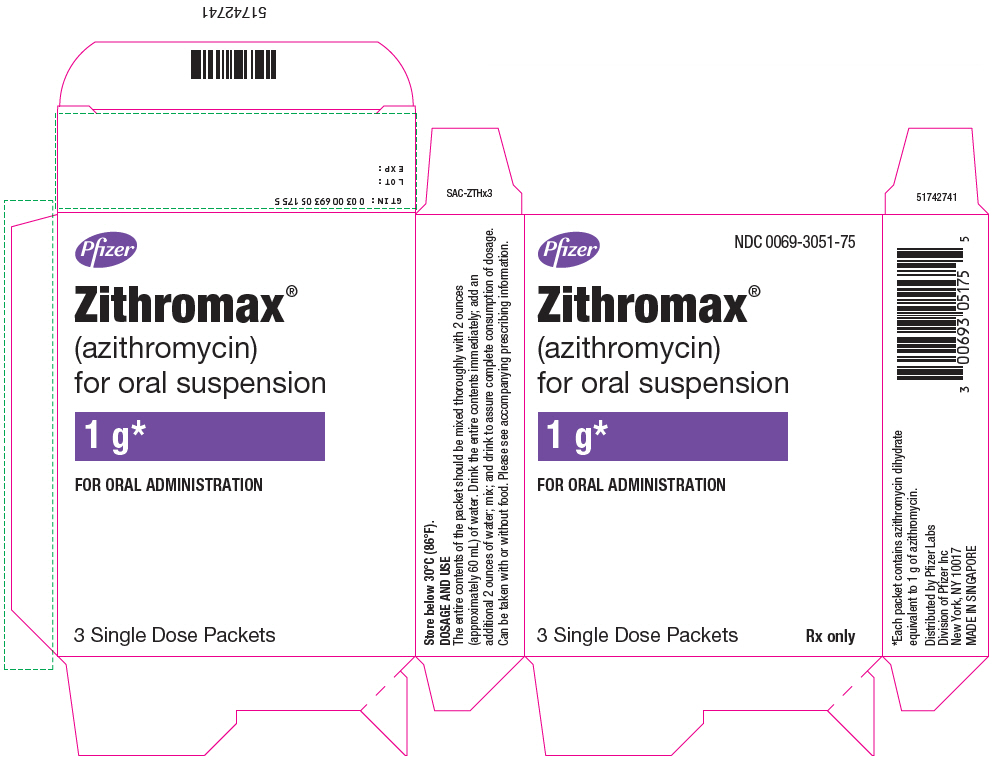 DRUG LABEL: ZITHROMAX
NDC: 0069-3080 | Form: TABLET, FILM COATED
Manufacturer: Pfizer Laboratories Div Pfizer Inc
Category: prescription | Type: HUMAN PRESCRIPTION DRUG LABEL
Date: 20250905

ACTIVE INGREDIENTS: AZITHROMYCIN DIHYDRATE 600 mg/1 1
INACTIVE INGREDIENTS: ANHYDROUS DIBASIC CALCIUM PHOSPHATE; CROSCARMELLOSE SODIUM; MAGNESIUM STEARATE; SODIUM LAURYL SULFATE; HYPROMELLOSE, UNSPECIFIED; TITANIUM DIOXIDE; LACTOSE, UNSPECIFIED FORM; TRIACETIN

HIGHLIGHTS OF PRESCRIBING INFORMATION

These highlights do not include all the information needed to use ZITHROMAX safely and effectively. See full prescribing information for ZITHROMAX.
ZITHROMAX® (azithromycin) 600 mg tablets, for oral use
ZITHROMAX® (azithromycin) for oral suspension
Initial U.S. Approval: 1991

1 INDICATIONS AND USAGE

ZITHROMAX is a macrolide antibacterial indicated for mild to moderate infections caused by designated, susceptible bacteria:

- Sexually Transmitted Diseases (1.1)
- Mycobacterial Infections (1.2)

To reduce the development of drug-resistant bacteria and maintain the effectiveness of ZITHROMAX and other antibacterial drugs, ZITHROMAX should be used only to treat or prevent infections that are proven or strongly suspected to be caused by susceptible bacteria. (1.3)

2 DOSAGE AND ADMINISTRATION

- Sexually Transmitted Diseases (2.1)
- Mycobacterial Infections (2.2)

3 DOSAGE FORMS AND STRENGTHS

- ZITHROMAX 600 mg tablets (3)
- ZITHROMAX for oral suspension 1000 mg/5 mL (3)

4 CONTRAINDICATIONS

- Patients with known hypersensitivity to azithromycin, erythromycin, any macrolide, or ketolide antibiotic. (4.1)
- Patients with a history of cholestatic jaundice/hepatic dysfunction associated with prior use of azithromycin. (4.2)

5 WARNINGS AND PRECAUTIONS

- Serious (including fatal) allergic and skin reactions. Discontinue ZITHROMAX and initiate appropriate therapy if reaction occurs. (5.1)
- Hepatotoxicity: Discontinue azithromycin immediately if signs and symptoms of hepatitis occur. (5.2)
- Infantile Hypertrophic Pyloric Stenosis (IHPS): Following the use of azithromycin in neonates (treatment up to 42 days of life), IHPS has been reported. Direct parents and caregivers to contact their physician if vomiting or irritability with feeding occurs. (5.3)
- Prolongation of QT interval and cases of torsades de pointes have been reported. This risk which can be fatal should be considered in patients with certain cardiovascular disorders including known QT prolongation or history torsades de pointes, those with proarrhythmic conditions, and with other drugs that prolong the QT interval. (5.4)
- Cardiovascular Death: Some observational studies have shown an approximately two-fold increased short-term potential risk of acute cardiovascular death in adults exposed to azithromycin relative to other antibacterial drugs, including amoxicillin. Consider balancing this potential risk with treatment benefits when prescribing ZITHROMAX. (5.5)
- Clostridioides difficile-Associated Diarrhea: Evaluate patients if diarrhea occurs. (5.6)
- ZITHROMAX may exacerbate muscle weakness in persons with myasthenia gravis. (5.7)

6 ADVERSE REACTIONS

The most common adverse reactions are diarrhea (5%), nausea (3%), abdominal pain (3%), or vomiting, (no percent given). (6)

To report SUSPECTED ADVERSE REACTIONS, contact Pfizer Inc at 1-800-438-1985 or FDA at 1-800-FDA-1088 or www.fda.gov/medwatch.

7 DRUG INTERACTIONS

- Nelfinavir: Close monitoring for known side effects of azithromycin, such as liver enzyme abnormalities and hearing impairment, is warranted. (7.1)
- Warfarin: Use with azithromycin may increase coagulation times; monitor prothrombin time. (7.2)

8 USE IN SPECIFIC POPULATIONS

- Pediatric Use: Safety and effectiveness in the treatment of patients under 6 months of age have not been established. (8.4)
- Geriatric Use: Elderly patients may be more susceptible to development of torsades de pointes arrhythmias. (8.5)

FULL PRESCRIBING INFORMATION

1 INDICATIONS AND USAGE

ZITHROMAX is a macrolide antibacterial drug indicated for the treatment of patients with mild to moderate infections caused by susceptible strains of the designated microorganisms in the specific conditions listed below.

1.1 Sexually Transmitted Diseases

Non-gonococcal urethritis and cervicitis due to Chlamydia trachomatis

1.2 Mycobacterial Infections

Prophylaxis of Disseminated Mycobacterium avium complex (MAC) Disease

ZITHROMAX, taken alone or in combination with rifabutin at its approved dose, is indicated for the prevention of disseminated MAC disease in persons with advanced HIV infection [see Dosage and Administration (2)].

Treatment of Disseminated MAC Disease

ZITHROMAX, taken in combination with ethambutol, is indicated for the treatment of disseminated MAC infections in persons with advanced HIV infection [see Use in Specific Populations (8.4) and Clinical Studies (14.1)].

1.3 Usage

To reduce the development of drug-resistant bacteria and maintain the effectiveness of ZITHROMAX and other antibacterial drugs, ZITHROMAX should be used only to treat infections that are proven or strongly suspected to be caused by susceptible bacteria. When culture and susceptibility information are available, they should be considered in selecting or modifying antibacterial therapy. In the absence of such data, local epidemiology and susceptibility patterns may contribute to the empiric selection of therapy.

2 DOSAGE AND ADMINISTRATION

[see Indications and Usage (1)]

ZITHROMAX for oral suspension (single dose 1 g packet) can be taken with or without food after constitution. However, increased tolerability has been observed when tablets are taken with food.

Zithromax for oral suspension (single dose 1 g packet) is not for pediatric use. For pediatric suspension see the prescribing information for ZITHROMAX (azithromycin for oral suspension) 100 mg/5 mL and 200 mg/5 mL bottles.

Directions for administration of ZITHROMAX for oral suspension in the single dose packet (1 g): The entire contents of the packet should be mixed thoroughly with two ounces (approximately 60 mL) of water. Drink the entire contents immediately; add an additional two ounces of water, mix, and drink to ensure complete consumption of dosage. The single dose packet should not be used to administer doses other than 1000 mg of azithromycin.

2.1 Sexually Transmitted Diseases

The recommended dose of ZITHROMAX for the treatment of non-gonococcal urethritis and cervicitis due to C. trachomatis is a single 1 gram (1000 mg) dose of ZITHROMAX. This dose can be administered as one single dose packet (1 g).

2.2 Mycobacterial Infections

Prevention of Disseminated MAC Infections

The recommended dose of ZITHROMAX for the prevention of disseminated Mycobacterium avium complex (MAC) disease is: 1200 mg taken once weekly. This dose of ZITHROMAX may be combined with the approved dosage regimen of rifabutin.

Treatment of Disseminated MAC Infections

ZITHROMAX should be taken at a daily dose of 600 mg, in combination with ethambutol at the recommended daily dose of 15 mg/kg. Other antimycobacterial drugs that have shown in vitro activity against MAC may be added to the regimen of azithromycin plus ethambutol at the discretion of the physician or health care provider.

3 DOSAGE FORMS AND STRENGTHS

ZITHROMAX 600 mg tablets (engraved on front with "PFIZER" and on back with "308") are supplied as white, modified oval-shaped, film-coated tablets containing azithromycin dihydrate equivalent to 600 mg azithromycin. These are packaged in bottles of 30 tablets.

ZITHROMAX for oral suspension 1000 mg/5 mL is supplied in single-dose packets containing azithromycin dihydrate equivalent to 1 gram of azithromycin.

4 CONTRAINDICATIONS

4.1 Hypersensitivity

ZITHROMAX is contraindicated in patients with known hypersensitivity to azithromycin, erythromycin, any macrolide, or ketolide drug.

4.2 Hepatic Dysfunction

ZITHROMAX is contraindicated in patients with a history of cholestatic jaundice/hepatic dysfunction associated with prior use of azithromycin.

5 WARNINGS AND PRECAUTIONS

5.1 Hypersensitivity

Serious allergic reactions, including angioedema, anaphylaxis, and dermatologic reactions including Acute Generalized Exanthematous Pustulosis (AGEP), Stevens-Johnson Syndrome, and toxic epidermal necrolysis, have been reported rarely in patients on azithromycin therapy. [see Contraindications (4.1)]

Fatalities have been reported. Cases of Drug Reaction with Eosinophilia and Systemic Symptoms (DRESS) have also been reported. Despite initially successful symptomatic treatment of the allergic symptoms, when symptomatic therapy was discontinued, the allergic symptoms recurred soon thereafter in some patients without further azithromycin exposure. These patients required prolonged periods of observation and symptomatic treatment. The relationship of these episodes to the long tissue half-life of azithromycin and subsequent prolonged exposure to antigen is presently unknown.

If an allergic reaction occurs, the drug should be discontinued and appropriate therapy should be instituted. Physicians should be aware that allergic symptoms may reappear when symptomatic therapy is discontinued.

5.2 Hepatotoxicity

Abnormal liver function, hepatitis, cholestatic jaundice, hepatic necrosis, and hepatic failure have been reported, some of which have resulted in death. Discontinue azithromycin immediately if signs and symptoms of hepatitis occur.

5.3 Infantile Hypertrophic Pyloric Stenosis (IHPS)

Following the use of azithromycin in neonates (treatment up to 42 days of life), IHPS has been reported. Direct parents and caregivers to contact their physician if vomiting or irritability with feeding occurs.

5.4 QT Prolongation

Prolonged cardiac repolarization and QT interval, imparting a risk of developing cardiac arrhythmia and torsades de pointes, have been seen with treatment with macrolides, including azithromycin. Cases of torsades de pointes have been spontaneously reported during postmarketing surveillance in patients receiving azithromycin. Providers should consider the risk of QT prolongation which can be fatal when weighing the risks and benefits of azithromycin for at-risk groups including:

- patients with known prolongation of the QT interval, a history of torsades de pointes, congenital long QT syndrome, bradyarrhythmias or uncompensated heart failure
- patients on drugs known to prolong the QT interval
- patients with ongoing proarrhythmic conditions such as uncorrected hypokalemia or hypomagnesemia, clinically significant bradycardia, and in patients receiving Class IA (quinidine, procainamide) or Class III (dofetilide, amiodarone, sotalol) antiarrhythmic agents.

Elderly patients may be more susceptible to drug-associated effects on the QT interval.

5.5 Cardiovascular Death

Some observational studies have shown an approximately two-fold increased short-term potential risk of acute cardiovascular death in adults exposed to azithromycin relative to other antibacterial drugs, including amoxicillin. The five-day cardiovascular mortality observed in these studies ranged from 20 to 400 per million azithromycin treatment courses. This potential risk was noted to be greater during the first five days of azithromycin use and does not appear to be limited to those patients with preexisting cardiovascular diseases. The data in these observational studies are insufficient to establish or exclude a causal relationship between acute cardiovascular death and azithromycin use. Consider balancing this potential risk with treatment benefits when prescribing ZITHROMAX.

5.6 Clostridioides difficile-Associated Diarrhea (CDAD)

CDAD has been reported with use of nearly all antibacterial agents, including ZITHROMAX, and may range in severity from mild diarrhea to fatal colitis. Treatment with antibacterial agents alters the normal flora of the colon, leading to overgrowth of C. difficile.

C. difficile produces toxins A and B which contribute to the development of CDAD. Hypertoxin-producing strains of C. difficile cause increased morbidity and mortality, as these infections can be refractory to antibacterial therapy and may require colectomy. CDAD must be considered in all patients who present with diarrhea following antibiotic use. Careful medical history is necessary since CDAD has been reported to occur over two months after the administration of antibacterial agents.

If CDAD is suspected or confirmed, ongoing antibiotic use not directed against C. difficile may need to be discontinued. Appropriate fluid and electrolyte management, protein supplementation, antibiotic treatment of C. difficile, and surgical evaluation should be instituted as clinically indicated.

5.7 Exacerbation of Myasthenia Gravis

Exacerbations of symptoms of myasthenia gravis and new onset of myasthenic syndrome have been reported in patients receiving azithromycin therapy.

5.8 Use in Sexually Transmitted Infections

ZITHROMAX, (single dose 1 g packet) at the recommended dose, should not be relied upon to treat gonorrhea or syphilis. Antibacterial agents used in high doses for short periods of time to treat non-gonococcal urethritis may mask or delay the symptoms of incubating gonorrhea or syphilis. All patients with sexually transmitted urethritis or cervicitis should have a serologic test for syphilis and appropriate cultures for gonorrhea performed at the time of diagnosis. Appropriate antibacterial therapy and follow-up tests for these diseases should be initiated if infection is confirmed.

5.9 Development of Drug-Resistant Bacteria

Prescribing ZITHROMAX in the absence of a proven or strongly suspected bacterial infection or a prophylactic indication is unlikely to provide benefit to the patient and increases the risk of the development of drug-resistant bacteria.

6 ADVERSE REACTIONS

The following clinically significant adverse reactions are described elsewhere in labeling:

- Hypersensitivity [see Warnings and Precautions (5.1)]
- Hepatotoxicity [see Warnings and Precautions (5.2)]
- Infantile Hypertrophic Pyloric Stenosis (IHPS) [see Warnings and Precautions (5.3)]
- QT Prolongation [see Warnings and Precautions (5.4)]
- Cardiovascular Death [see Warnings and Precautions (5.5)]
- Clostridioides difficile-Associated Diarrhea (CDAD) [see Warnings and Precautions (5.6)]
- Exacerbation of Myasthenia Gravis [see Warnings and Precautions (5.7)]

6.1 Clinical Trials Experience

Because clinical trials are conducted under widely varying conditions, adverse reaction rates observed in the clinical trials of a drug cannot be directly compared to rates in the clinical trials of another drug and may not reflect the rates observed in practice.

In clinical trials, most of the reported adverse reactions were mild to moderate in severity and were reversible upon discontinuation of the drug. Approximately 0.7% of the patients from the multiple-dose clinical trials discontinued ZITHROMAX (azithromycin) therapy because of treatment-related adverse reactions. Serious adverse reactions included angioedema and cholestatic jaundice. Most of the adverse reactions leading to discontinuation were related to the gastrointestinal tract, e.g., nausea, vomiting, diarrhea, or abdominal pain. [see Clinical Studies (14.2)]

Multiple-dose regimen

Overall, the most common adverse reactions in adult patients receiving a multiple-dose regimen of ZITHROMAX were related to the gastrointestinal system with diarrhea/loose stools (5%), nausea (3%), and abdominal pain (3%) being the most frequently reported.

No other adverse reactions occurred in patients on the multiple-dose regimen of ZITHROMAX with a frequency greater than 1%. Adverse reactions that occurred with a frequency of 1% or less included the following:

Cardiovascular: Palpitations and chest pain.

Gastrointestinal: Dyspepsia, flatulence, vomiting, melena, and cholestatic jaundice.

Genitourinary: Monilia, vaginitis, and nephritis.

Nervous System: Dizziness, headache, vertigo, and somnolence.

General: Fatigue.

Allergic: Rash, photosensitivity, and angioedema.

Chronic therapy with 1200 mg weekly regimen

The nature of adverse reactions seen with the 1200 mg weekly dosing regimen for the prevention of Mycobacterium avium infection in severely immunocompromised HIV-infected patients were similar to those seen with short-term dosing regimens. [see Clinical Studies (14)]

Chronic therapy with 600 mg daily regimen combined with ethambutol

The nature of adverse reactions seen with the 600 mg daily dosing regimen for the treatment of Mycobacterium avium complex infection in severely immunocompromised HIV-infected patients were similar to those seen with short term dosing regimens. Five percent of patients experienced reversible hearing impairment in the pivotal clinical trial for the treatment of disseminated MAC in patients with AIDS. Hearing impairment has been reported with macrolide antibiotics, especially at higher doses. Other treatment-related adverse reactions occurring in >5% of subjects and seen at any time during a median of 87.5 days of therapy include: abdominal pain (14%), nausea (14%), vomiting (13%), diarrhea (12%), flatulence (5%), headache (5%), and abnormal vision (5%). Discontinuations from treatment due to laboratory abnormalities or adverse reactions considered related to study drug occurred in 8 of 88 (9.1%) of subjects.

Single 1 gram dose regimen

Overall, the most common adverse reactions in patients receiving a single-dose regimen of 1 gram of ZITHROMAX were related to the gastrointestinal system and were more frequently reported than in patients receiving the multiple-dose regimen.

Adverse reactions that occurred in patients on the single 1 gram dosing regimen of ZITHROMAX with a frequency of 1% or greater included diarrhea/loose stools (7%), nausea (5%), abdominal pain (5%), vomiting (2%), dyspepsia (1%), and vaginitis (1%).

6.2 Postmarketing Experience

The following adverse reactions have been identified during post approval use of azithromycin. Because these reactions are reported voluntarily from a population of uncertain size, it is not always possible to reliably estimate their frequency or establish a causal relationship to drug exposure.

Adverse reactions reported with azithromycin during the postmarketing period in adult and/or pediatric patients for which a causal relationship may not be established include:

Allergic: Arthralgia, edema, urticaria, and angioedema.

Cardiovascular: Arrhythmias, including ventricular tachycardia, and hypotension. There have been reports of QT prolongation, torsades de pointes, and cardiovascular death.

Gastrointestinal: Anorexia, constipation, dyspepsia, flatulence, vomiting/diarrhea pseudomembranous colitis, pancreatitis, oral candidiasis, pyloric stenosis, and tongue discoloration.

General: Asthenia, paresthesia, fatigue, malaise, and anaphylaxis.

Genitourinary: Interstitial nephritis, acute renal failure, and vaginitis.

Hematopoietic: Thrombocytopenia.

Liver/Biliary: Abnormal liver function, hepatitis, cholestatic jaundice, hepatic necrosis, and hepatic failure. [see Warnings and Precautions (5.2)]

Nervous System: Convulsions, dizziness/vertigo, headache, somnolence, hyperactivity, nervousness, agitation, and syncope.

Psychiatric: Aggressive reaction and anxiety.

Skin/Appendages: Pruritus, and serious skin reactions including erythema multiforme, AGEP, Stevens-Johnson Syndrome, toxic epidermal necrolysis, and DRESS.

Special Senses: Hearing disturbances including hearing loss, deafness, and/or tinnitus, and reports of taste/smell perversion and/or loss.

6.3 Laboratory Abnormalities

Significant abnormalities (irrespective of drug relationship) occurring during the clinical trials were reported as follows:

- With an incidence of 1–2%, elevated serum creatine phosphokinase, potassium, ALT (SGPT), GGT, and AST (SGOT).
- With an incidence of less than 1%, leukopenia, neutropenia, decreased platelet count, elevated serum alkaline phosphatase, bilirubin, BUN, creatinine, blood glucose, LDH, and phosphate.

When follow-up was provided, changes in laboratory tests appeared to be reversible.

In multiple-dose clinical trials involving more than 3000 patients, 3 patients discontinued therapy because of treatment-related liver enzyme abnormalities and 1 because of a renal function abnormality.

In a phase 1 drug interaction study performed in normal volunteers, 1 of 6 subjects given the combination of azithromycin and rifabutin, 1 of 7 given rifabutin alone, and 0 of 6 given azithromycin alone developed a clinically significant neutropenia (<500 cells/mm^3).

Laboratory abnormalities seen in clinical trials for the prevention of disseminated Mycobacterium avium disease in severely immunocompromised HIV-infected patients. [see Clinical Studies (14)]

Chronic therapy (median duration: 87.5 days, range: 1–229 days) that resulted in laboratory abnormalities in >5% of subjects with normal baseline values in the pivotal trial for treatment of disseminated MAC in severely immunocompromised HIV-infected patients treated with azithromycin 600 mg daily in combination with ethambutol include: a reduction in absolute neutrophils to <50% of the lower limit of normal (10/52, 19%) and an increase to five times the upper limit of normal in alkaline phosphatase (3/35, 9%). These findings in subjects with normal baseline values are similar when compared to all subjects for analyses of neutrophil reductions (22/75, 29%) and elevated alkaline phosphatase (16/80, 20%). Causality of these laboratory abnormalities due to the use of study drug has not been established.

7 DRUG INTERACTIONS

7.1 Nelfinavir

Co-administration of nelfinavir at steady-state with a single oral dose of azithromycin resulted in increased azithromycin serum concentrations. Although a dose adjustment of azithromycin is not recommended when administered in combination with nelfinavir, close monitoring for known adverse reactions of azithromycin, such as liver enzyme abnormalities and hearing impairment, is warranted. [see Adverse Reactions (6)]

7.2 Warfarin

Spontaneous postmarketing reports suggest that concomitant administration of azithromycin may potentiate the effects of oral anticoagulants such as warfarin, although the prothrombin time was not affected in the dedicated drug interaction study with azithromycin and warfarin. Prothrombin times should be carefully monitored while patients are receiving azithromycin and oral anticoagulants concomitantly.

7.3 Potential Drug-Drug Interaction with Macrolides

Interactions with digoxin, colchicine or phenytoin have not been reported in clinical trials with azithromycin. No specific drug interaction studies have been performed to evaluate potential drug-drug interaction. However, drug interactions have been observed with other macrolide products. Until further data are developed regarding drug interactions when digoxin, colchicine or phenytoin are used with azithromycin careful monitoring of patients is advised.

8 USE IN SPECIFIC POPULATIONS

8.1 Pregnancy

TERATOGENIC EFFECTS

Risk Summary

Available data from published literature and postmarketing experience over several decades with azithromycin use in pregnant women have not identified any drug-associated risks for major birth defects, miscarriage, or adverse maternal or fetal outcomes (see Data).

Developmental toxicity studies with azithromycin in rats, mice, and rabbits showed no drug-induced fetal malformations at doses up to 3, 2, and 1 times, respectively, an adult human daily dose of 600 mg based on body surface area. Decreased viability and delayed development were observed in the offspring of pregnant rats administered azithromycin from day 6 of pregnancy through weaning at a dose equivalent to 3 times an adult human daily dose of 600 mg based on body surface area (see Data).

The estimated background risk of major birth defects and miscarriage for the indicated populations is unknown. All pregnancies have a background risk of birth defect, loss, or other adverse outcomes. In the U.S. general population, the estimated background risk of major birth defects and miscarriage in clinically recognized pregnancies is 2 to 4% and 15 to 20%, respectively.

Data

Human Data

Available data from published observational studies, case series, and case reports over several decades do not suggest an increased risk for major birth defects, miscarriage, or adverse maternal or fetal outcomes with azithromycin use in pregnant women. Limitations of these data include the lack of randomization and inability to control for confounders such as underlying maternal disease and maternal use of concomitant medications.

Animal Data

Azithromycin administered during the period of organogenesis did not cause fetal malformations in rats and mice at oral doses up to 200 mg/kg/day (moderately maternally toxic). Based on body surface area, this dose is approximately 3 (rats) and 2 (mice) times an adult human daily dose of 600 mg. In rabbits administered azithromycin at oral doses of 10, 20, and 40 mg/kg/day during organogenesis, reduced maternal body weight and food consumption were observed in all groups; no evidence of fetotoxicity or teratogenicity was observed at these doses, the highest of which is approximately equal to an adult human daily dose of 600 mg based on body surface area.

In a pre- and postnatal development study, azithromycin was administered orally to pregnant rats from day 6 of pregnancy until weaning at doses of 50 or 200 mg/kg/day. Maternal toxicity (reduced food consumption and body weight gain; increased stress at parturition) was observed at the higher dose. Effects in the offspring were noted at 200 mg/kg/day during the postnatal development period (decreased viability, delayed developmental landmarks). These effects were not observed in a pre- and postnatal rat study when up to 200 mg/kg/day of azithromycin was given orally beginning on day 15 of pregnancy until weaning.

8.2 Lactation

Risk Summary

Azithromycin is present in human milk (see Data). Non-serious adverse reactions have been reported in breastfed infants after maternal administration of azithromycin (see Clinical Considerations). There are no available data on the effects of azithromycin on milk production. The developmental and health benefits of breastfeeding should be considered along with the mother's clinical need for ZITHROMAX and any potential adverse effects on the breastfed infant from ZITHROMAX or from the underlying maternal condition.

Clinical Considerations

Advise women to monitor the breastfed infant for diarrhea, vomiting, or rash.

Data

Azithromycin breastmilk concentrations were measured in 20 women after receiving a single 2 g oral dose of azithromycin during labor. Breastmilk samples collected on days 3 and 6 postpartum as well as 2 and 4 weeks postpartum revealed the presence of azithromycin in breastmilk up to 4 weeks after dosing. In another study, a single dose of azithromycin 500 mg was administered intravenously to 8 women prior to incision for cesarean section. Breastmilk (colostrum) samples obtained between 12 and 48 hours after dosing revealed that azithromycin persisted in breastmilk up to 48 hours.

8.4 Pediatric Use

In controlled clinical studies, azithromycin has been administered to pediatric patients ranging in age from 6 months to 12 years. For information regarding the use of ZITHROMAX (azithromycin for oral suspension) in the treatment of pediatric patients, [see Indications and Usage (1) and Dosage and Administration (2)] of the prescribing information for ZITHROMAX (azithromycin for oral suspension) 100 mg/5 mL and 200 mg/5 mL bottles.

HIV-Infected Pediatric Patients: The safety and efficacy of azithromycin for the prevention or treatment of MAC in HIV-infected children have not been established. Safety data are available for 72 children 5 months to 18 years of age (mean 7 years) who received azithromycin for treatment of opportunistic infections. The mean duration of therapy was 242 days (range 3–2004 days) at doses of <1 to 52 mg/kg/day (mean 12 mg/kg/day). Adverse reactions were similar to those observed in the adult population, most of which involved the gastrointestinal tract. Treatment-related reversible hearing impairment in children was observed in 4 subjects (5.6%). Two (2.8%) children prematurely discontinued treatment due to adverse reactions: one due to back pain and one due to abdominal pain, hot and cold flushes, dizziness, headache, and numbness. A third child discontinued due to a laboratory abnormality (eosinophilia). The protocols upon which these data are based specified a daily dose of 10–20 mg/kg/day (oral and/or IV) of azithromycin.

8.5 Geriatric Use

In multiple-dose clinical trials of oral azithromycin, 9% of patients were at least 65 years of age (458/4949) and 3% of patients (144/4949) were at least 75 years of age. No overall differences in safety or effectiveness were observed between these subjects and younger subjects, and other reported clinical experience has not identified differences in responses between the elderly and younger patients, but greater sensitivity of some older individuals cannot be ruled out.

Elderly patients may be more susceptible to development of torsades de pointes arrhythmias than younger patients. [see Warnings and Precautions (5.4)]

ZITHROMAX 600 mg tablets contain 2.1 mg of sodium per tablet. ZITHROMAX for oral suspension 1 gram single-dose packets contain 37.0 mg of sodium per packet.

Geriatric Patients with Opportunistic Infections, Including (MAC) Disease: Safety data are available for 30 patients (65–94 years old) treated with azithromycin at doses >300 mg/day for a mean of 207 days. These patients were treated for a variety of opportunistic infections, including MAC. The adverse reaction were generally similar to that seen in younger patients, except for a higher incidence of adverse reactions relating to the gastrointestinal system and to reversible impairment of hearing. [see Dosage and Administration (2)]

10 OVERDOSAGE

Adverse reactions experienced in higher than recommended doses were similar to those seen at normal doses. In the event of overdosage, general symptomatic and supportive measures are indicated as required.

11 DESCRIPTION

ZITHROMAX (azithromycin tablets and oral suspension) contains the active ingredient azithromycin, a macrolide antibacterial drug, for oral administration. Azithromycin has the chemical name (2R,3S,4R,5R,8R,10R,11R,12S,13S,14R)-13-[(2,6-dideoxy-3-C-methyl-3-O-methyl-α-L-ribo-hexopyranosyl)oxy]-2-ethyl- 3,4,10-trihydroxy-3,5,6,8,10,12,14-heptamethyl-11-[[3,4,6- trideoxy-3-(dimethylamino)-β-D-xylo-hexopyranosyl]oxy]-1-oxa-6-azacyclopentadecan-15-one. Azithromycin is derived from erythromycin; however, it differs chemically from erythromycin in that a methyl-substituted nitrogen atom is incorporated into the lactone ring. Its molecular formula is C38H72N2O12, and its molecular weight is 749.0. Azithromycin has the following structural formula:

Azithromycin, as the dihydrate, is a white crystalline powder with a molecular formula of C38H72N2O12∙2H2O and a molecular weight of 785.0.

ZITHROMAX tablets contain azithromycin dihydrate equivalent to 600 mg azithromycin. They also contain the following inactive ingredients: dibasic calcium phosphate anhydrous, pregelatinized starch, sodium croscarmellose, magnesium stearate, sodium lauryl sulfate, and an aqueous film coat consisting of hypromellose, titanium dioxide, lactose, and triacetin.

ZITHROMAX for oral suspension is supplied in a single-dose packet containing azithromycin dihydrate equivalent to 1 g azithromycin. It also contains the following inactive ingredients: colloidal silicon dioxide, sodium phosphate tribasic, anhydrous; spray dried artificial banana flavor, spray dried artificial cherry flavor, and sucrose.

12 CLINICAL PHARMACOLOGY

12.1 Mechanism of Action

Azithromycin is a macrolide antibacterial drug. [see Microbiology (12.4)]

12.2 Pharmacodynamics

Based on animal models of infection, the antibacterial activity of azithromycin appears to correlate with the ratio of area under the concentration-time curve to minimum inhibitory concentration (AUC/MIC) for certain pathogens (S. pneumoniae and S. aureus). The principal pharmacokinetic/pharmacodynamic parameter best associated with clinical and microbiological cure has not been elucidated in clinical trials with azithromycin.

Cardiac Electrophysiology

QTc interval prolongation was studied in a randomized, placebo-controlled parallel trial in 116 healthy subjects who received either chloroquine (1000 mg) alone or in combination with oral azithromycin (500 mg, 1000 mg, and 1500 mg once daily). Co-administration of azithromycin increased the QTc interval in a dose- and concentration- dependent manner. In comparison to chloroquine alone, the maximum mean (95% upper confidence bound) increases in QTcF were 5 (10) ms, 7 (12) ms and 9 (14) ms with the co-administration of 500 mg, 1000 mg and 1500 mg azithromycin, respectively.

12.3 Pharmacokinetics

The pharmacokinetic parameters of azithromycin in plasma after dosing as per labeled recommendations in healthy young adults and asymptomatic HIV-positive adults (age 18–40 years old) are portrayed in the following chart:

MEAN (CV%) PK PARAMETER
DOSE/DOSAGE FORM (serum, except as indicated) | Subjects | Day No. | Cmax (mcg/mL) | Tmax (hr) | C24 (mcg/mL) | AUC (mcg∙hr/mL) | T½ (hr) | Urinary Excretion (% of dose)
500 mg/250 mg capsule | 12 | 1 | 0.41 | 2.5 | 0.05 | 2.6 [AUC0–24;] | – | 4.5
and 250 mg on Days 2–5 | 12 | 5 | 0.24 | 3.2 | 0.05 | 2.1 | – | 6.5
1200 mg/600 mg tablets | 12 | 1 | 0.66 | 2.5 | 0.074 | 6.8 [0–last.] | 40 | –
%CV |  |  | (62%) | (79%) | (49%) | (64%) | (33%)
600 mg tablet/day | 7 | 1 | 0.33 | 2.0 | 0.039 | 2.4
%CV |  |  | 25% | (50%) | (36%) | (19%)
 | 7 | 22 | 0.55 | 2.1 | 0.14 | 5.8 | 84.5 | -
%CV |  |  | (18%) | (52%) | (26%) | (25%) |  | -
600 mg tablet/day (leukocytes) | 7 | 22 | 252 | 10.9 | 146 | 4763 | 82.8 | -
%CV |  |  | (49%) | (28%) | (33%) | (42%) | - | -

With a regimen of 500 mg on Day 1 and 250 mg/day on Days 2–5, Cmin and Cmax remained essentially unchanged from Day 2 through Day 5 of therapy. However, without a loading dose, azithromycin Cmin levels required 5 to 7 days to reach steady state.

In asymptomatic HIV-positive adult subjects receiving 600 mg ZITHROMAX tablets once daily for 22 days, steady state azithromycin serum levels were achieved by Day 15 of dosing.

The high values in adults for apparent steady-state volume of distribution (31.1 L/kg) and plasma clearance (630 mL/min) suggest that the prolonged half-life is due to extensive uptake and subsequent release of drug from tissues.

Absorption

The 1 gram single-dose packet is bioequivalent to four 250 mg azithromycin capsule.

When the oral suspension of azithromycin was administered with food, the Cmax increased by 46% and the AUC by 14%.

The absolute bioavailability of two 600 mg tablets was 34% (CV=56%). Administration of two 600 mg tablets with food increased Cmax by 31% (CV=43%) while the extent of absorption (AUC) was unchanged (mean ratio of AUCs=1.00; CV=55%).

Distribution

The serum protein binding of azithromycin is variable in the concentration range approximating human exposure, decreasing from 51% at 0.02 µg/mL to 7% at 2 µg/mL.

The antibacterial activity of azithromycin is pH related and appears to be reduced with decreasing pH. However, the extensive distribution of drug to tissues may be relevant to clinical activity.

Azithromycin has been shown to penetrate into tissues in humans, including skin, lung, tonsil, and cervix. Extensive tissue distribution was confirmed by examination of additional tissues and fluids (bone, ejaculum, prostate, ovary, uterus, salpinx, stomach, liver, and gallbladder). As there are no data from adequate and well-controlled studies of azithromycin treatment of infections in these additional body sites, the clinical importance of these tissue concentration data is unknown.

Azithromycin concentrates in phagocytes and fibroblasts as demonstrated by in vitro incubation techniques. Using such methodology, the ratio of intracellular to extracellular concentration was >30 after one hr of incubation. In vivo studies suggest that concentration in phagocytes may contribute to drug distribution to inflamed tissues.

Following oral administration of a single 1200 mg dose (two 600 mg tablets), the mean maximum concentration in peripheral leukocytes was 140 µg/mL. Concentration remained above 32 µg/mL, for approximately 60 hr. The mean half-lives for 6 males and 6 females were 34 hr and 57 hr, respectively. Leukocyte-to-plasma Cmax ratios for males and females were 258 (±77%) and 175 (±60%), respectively, and the AUC ratios were 804 (±31%) and 541 (±28%) respectively. The clinical relevance of these findings is unknown.

Following oral administration of multiple daily doses of 600 mg (1 tablet/day) to asymptomatic HIV-positive adults, mean maximum concentration in peripheral leukocytes was 252 µg/mL (±49%). Trough concentrations in peripheral leukocytes at steady-state averaged 146 µg/mL (±33%). The mean leukocyte-to-serum Cmax ratio was 456 (±38%) and the mean leukocyte to serum AUC ratio was 816 (±31%). The clinical relevance of these findings is unknown.

Metabolism

In vitro and in vivo studies to assess the metabolism of azithromycin have not been performed.

Elimination

Plasma concentrations of azithromycin following single 500 mg oral and IV doses declined in a polyphasic pattern resulting in an average terminal half-life of 68 hr. Biliary excretion of azithromycin, predominantly as unchanged drug, is a major route of elimination. Over the course of a week, approximately 6% of the administered dose appears as unchanged drug in urine.

Specific Populations

Patients with Renal Impairment

Azithromycin pharmacokinetics was investigated in 42 adults (21 to 85 years of age) with varying degrees of renal impairment. Following the oral administration of a single 1.0 g dose of azithromycin (4 × 250 mg capsules), the mean Cmax and AUC0–120 increased by 5.1% and 4.2%, respectively, in subjects with GFR 10 to 80 mL/min compared to subjects with normal renal function (GFR >80 mL/min). The mean Cmax and AUC0–120 increased 61% and 35%, respectively, in subjects with end-stage renal disease (GFR <10 mL/min) compared to subjects with normal renal function (GFR >80 mL/min).

Patients with Hepatic Impairment

The pharmacokinetics of azithromycin in subjects with hepatic impairment has not been established.

Male and Female Patients

There are no significant differences in the disposition of azithromycin between male and female subjects. No dosage adjustment is recommended on the basis of gender.

Geriatric Patients

Pharmacokinetic parameters in older volunteers (65 to 85 years old) were similar to those in younger volunteers (18 to 40 years old) for the 5-day therapeutic regimen. Dosage adjustment does not appear to be necessary for older patients with normal renal and hepatic function receiving treatment with this dosage regimen. [see Geriatric Use (8.5)]

Pediatric Patients

For information regarding the pharmacokinetics of ZITHROMAX (azithromycin for oral suspension) in pediatric patients, see the prescribing information for ZITHROMAX (azithromycin for oral suspension) 100 mg/5 mL and 200 mg/5 mL bottles.

Drug Interaction Studies

Drug interaction studies were performed with azithromycin and other drugs likely to be co-administered. The effects of co-administration of azithromycin on the pharmacokinetics of other drugs are shown in Table 1 and the effects of other drugs on the pharmacokinetics of azithromycin are shown in Table 2.

Co-administration of azithromycin at therapeutic doses had a modest effect on the pharmacokinetics of the drugs listed in Table 1. No dosage adjustment of drugs listed in Table 1 is recommended when co-administered with azithromycin.

Co-administration of azithromycin with efavirenz or fluconazole had a modest effect on the pharmacokinetics of azithromycin. Nelfinavir significantly increased the Cmax and AUC of azithromycin. No dosage adjustment of azithromycin is recommended when administered with drugs listed in Table 2. [see Drug Interactions (7.3)]

Table 1. Drug Interactions: Pharmacokinetic Parameters for Co-administered Drugs in the Presence of Azithromycin
Co-administered Drug | Dose of Co-administered Drug | Dose of Azithromycin | n | Ratio (with/without azithromycin) of Co-administered Drug Pharmacokinetic Parameters (90% CI); No Effect = 1.00
Co-administered Drug | Dose of Co-administered Drug | Dose of Azithromycin | n | Mean Cmax | Mean AUC
Atorvastatin | 10 mg/day for 8 days | 500 mg/day orally on days 6–8 | 12 | 0.83 (0.63 to 1.08) | 1.01 (0.81 to 1.25)
Carbamazepine | 200 mg/day for 2 days, then 200 mg twice a day for 18 days | 500 mg/day orally for days 16–18 | 7 | 0.97 (0.88 to 1.06) | 0.96 (0.88 to 1.06)
Cetirizine | 20 mg/day for 11 days | 500 mg orally on day 7, then 250 mg/day on days 8–11 | 14 | 1.03 (0.93 to 1.14) | 1.02 (0.92 to 1.13)
Didanosine | 200 mg orally twice a day for 21 days | 1,200 mg/day orally on days 8–21 | 6 | 1.44 (0.85 to 2.43) | 1.14 (0.83 to 1.57)
Efavirenz | 400 mg/day for 7 days | 600 mg orally on day 7 | 14 | 1.04 [- 90% Confidence interval not reported] | 0.95
Fluconazole | 200 mg orally single dose | 1,200 mg orally single dose | 18 | 1.04 (0.98 to 1.11) | 1.01 (0.97 to 1.05)
Indinavir | 800 mg three times a day for 5 days | 1,200 mg orally on day 5 | 18 | 0.96 (0.86 to 1.08) | 0.90 (0.81 to 1.00)
Midazolam | 15 mg orally on day 3 | 500 mg/day orally for 3 days | 12 | 1.27 (0.89 to 1.81) | 1.26 (1.01 to 1.56)
Nelfinavir | 750 mg three times a day for 11 days | 1,200 mg orally on day 9 | 14 | 0.90 (0.81 to 1.01) | 0.85 (0.78 to 0.93)
Sildenafil | 100 mg on days 1 and 4 | 500 mg/day orally for 3 days | 12 | 1.16 (0.86 to 1.57) | 0.92 (0.75 to 1.12)
Theophylline | 4 mg/kg IV on days 1, 11, 25 | 500 mg orally on day 7, 250 mg/day on days 8–11 | 10 | 1.19 (1.02 to 1.40) | 1.02 (0.86 to 1.22)
Theophylline | 300 mg orally BID ×15 days | 500 mg orally on day 6, then 250 mg/day on days 7–10 | 8 | 1.09 (0.92 to 1.29) | 1.08 (0.89 to 1.31)
Triazolam | 0.125 mg on day 2 | 500 mg orally on day 1, then 250 mg/day on day 2 | 12 | 1.06 | 1.02
Trimethoprim/ Sulfamethoxazole | 160 mg/800 mg/day orally for 7 days | 1,200 mg orally on day 7 | 12 | 0.85 (0.75 to 0.97)/ 0.90 (0.78 to 1.03) | 0.87 (0.80 to 0.95/ 0.96 (0.88 to 1.03)
Zidovudine | 500 mg/day orally for 21 days | 600 mg/day orally for 14 days | 5 | 1.12 (0.42 to 3.02) | 0.94 (0.52 to 1.70)
Zidovudine | 500 mg/day orally for 21 days | 1,200 mg/day orally for 14 days | 4 | 1.31 (0.43 to 3.97) | 1.30 (0.69 to 2.43)

Table 2. Drug Interactions: Pharmacokinetic Parameters for Azithromycin in the Presence of Co-administered Drugs. [see Drug Interactions (7.3)]
Co-administered Drug | Dose of Co-administered Drug | Dose of Azithromycin | n | Ratio (with/without co-administered drug) of Azithromycin Pharmacokinetic Parameters (90% CI); No Effect = 1.00
Co-administered Drug | Dose of Co-administered Drug | Dose of Azithromycin | n | Mean Cmax | Mean AUC
Efavirenz | 400 mg/day for 7 days | 600 mg orally on day 7 | 14 | 1.22 (1.04 to 1.42) | 0.92 [- 90% Confidence interval not reported]
Fluconazole | 200 mg orally single dose | 1,200 mg orally single dose | 18 | 0.82 (0.66 to 1.02) | 1.07 (0.94 to 1.22)
Nelfinavir | 750 mg three times a day for 11 days | 1,200 mg orally on day 9 | 14 | 2.36 (1.77 to 3.15) | 2.12 (1.80 to 2.50)

12.4 Microbiology

Mechanism of Action

Azithromycin acts by binding to the 23S rRNA of the 50S ribosomal subunit of susceptible microorganisms inhibiting bacterial protein synthesis and impeding the assembly of the 50S ribosomal subunit.

Resistance

The most frequently encountered mechanism of resistance to azithromycin is modification of the 23S rRNA target, most often by methylation. Ribosomal modifications can determine cross resistance to other macrolides, lincosamides, and streptogramin B (MLSB phenotype). The mechanism of acquired mutational resistance in isolates of Mycobacterium avium complex (i.e., 23S rRNA genemutation) is the same for both clarithromycin and azithromycin.

Antimicrobial Activity

Azithromycin has been shown to be active against the following microorganisms, both in vitro and in clinical infections. [see Indications and Usage (1)]

Mycobacteria

Mycobacterium avium complex (MAC) consisting of:
Mycobacterium avium
Mycobacterium intracellulare

Other Microorganisms

Chlamydia trachomatis

Susceptibility Testing

For specific information regarding susceptibility test interpretive criteria and associated test methods and quality control standards recognized by FDA for this drug, please see: https://www.fda.gov/STIC.

13 NONCLINICAL TOXICOLOGY

13.1 Carcinogenesis, Mutagenesis, Impairment of Fertility

Long-term studies in animals have not been performed to evaluate carcinogenic potential. Azithromycin has shown no mutagenic potential in standard laboratory tests: mouse lymphoma assay, human lymphocyte clastogenic assay, and mouse bone marrow clastogenic assay. In fertility studies conducted in male and female rats, oral administration of azithromycin for 64 to 66 days (males) or 15 days (females) prior to and during cohabitation resulted in decreased pregnancy rate at 20 and 30 mg/kg/day when both males and females were treated with azithromycin. This minimal effect on pregnancy rate (approximately 12% reduction compared to concurrent controls) did not become more pronounced when the dose was increased from 20 to 30 mg/kg/day (approximately 0.3 to 0.5 times the adult human daily dose of 600 mg based on body surface area) and it was not observed when only one animal in the mated pair was treated. There were no effects on any other reproductive parameters, and there were no effects on fertility at 10 mg/kg/day. The relevance of these findings to patients being treated with azithromycin at the doses and durations recommended in the prescribing information is uncertain.

13.2 Animal Toxicology

Phospholipidosis (intracellular phospholipid accumulation) has been observed in some tissues of mice, rats, and dogs given multiple doses of azithromycin. It has been demonstrated in numerous organ systems (e.g., eye, dorsal root ganglia, liver, gallbladder, kidney, spleen, and/or pancreas) in dogs and rats treated with azithromycin at doses which, expressed on the basis of body surface area, are similar to or less than the highest recommended adult human dose. This effect has been shown to be reversible after cessation of azithromycin treatment. Based on the pharmacokinetic data, phospholipidosis has been seen in the rat (50 mg/kg/day dose) at the observed maximal plasma concentration of 1.3 mcg/mL (1.6 times the observed Cmax of 0.821 mcg/mL at the adult dose of 2 g.) Similarly, it has been shown in the dog (10 mg/kg/day dose) at the observed maximal serum concentration of 1 mcg/mL (1.2 times the observed Cmax of 0.821 mcg/mL at the adult dose of 2 g).

Phospholipidosis was also observed in neonatal rats dosed for 18 days at 30 mg/kg/day, which is less than the pediatric dose of 60 mg/kg based on the surface area. It was not observed in neonatal rats treated for 10 days at 40 mg/kg/day with mean maximal serum concentrations of 1.86 mcg/mL, approximately 1.5 times the Cmax of 1.27 mcg/mL at the pediatric dose. Phospholipidosis has been observed in neonatal dogs (10 mg/kg/day) at maximum mean whole blood concentrations of 3.54 mcg/mL, approximately 3 times the pediatric dose Cmax.

The significance of the finding for animals and for humans is unknown.

14 CLINICAL STUDIES

14.1 Clinical Studies in Patients with Advanced HIV Infection for the Prevention and Treatment of Disease Due to Disseminated Mycobacterium avium Complex (MAC)

[see Indications and Usage (1)]

Prevention of Disseminated MAC Disease

Two randomized, double-blind clinical trials were performed in patients with CD4 counts <100 cells/µL. The first trial (Study 155) compared azithromycin (1200 mg once weekly) to placebo and enrolled 182 patients with a mean CD4 count of 35 cells/mcgL. The second trial (Study 174) randomized 723 patients to either azithromycin (1200 mg once weekly), rifabutin (300 mg daily), or the combination of both. The mean CD4 count was 51 cells/mcgL. The primary endpoint in these trials was disseminated MAC disease. Other endpoints included the incidence of clinically significant MAC disease and discontinuations from therapy for drug-related side effects.

MAC bacteremia

In Study 155, 85 patients randomized to receive azithromycin and 89 patients randomized to receive placebo met the entrance criteria. Cumulative incidences at 6, 12, and 18 months of the possible outcomes are in the following table:

Cumulative Incidence Rate, %: Placebo (n=89)
Month | MAC Free and Alive | MAC | Adverse Experience | Lost to Follow-up
6 | 69.7 | 13.5 | 6.7 | 10.1
12 | 47.2 | 19.1 | 15.7 | 18.0
18 | 37.1 | 22.5 | 18.0 | 22.5
Cumulative Incidence Rate, %: Azithromycin (n=85)
Month | MAC Free and Alive | MAC | Adverse Experience | Lost to Follow-up
6 | 84.7 | 3.5 | 9.4 | 2.4
12 | 63.5 | 8.2 | 16.5 | 11.8
18 | 44.7 | 11.8 | 25.9 | 17.6

The difference in the one-year cumulative incidence rates of disseminated MAC disease (placebo – azithromycin) is 10.9%. This difference is statistically significant (p=0.037) with a 95% confidence interval for this difference of 0.8%, 20.9%. The comparable number of patients experiencing adverse events and the fewer number of patients lost to follow-up on azithromycin should be taken into account when interpreting the significance of this difference.

In Study 174, 223 patients randomized to receive rifabutin, 223 patients randomized to receive azithromycin, and 218 patients randomized to receive both rifabutin and azithromycin met the entrance criteria. Cumulative incidences at 6, 12, and 18 months of the possible outcomes are recorded in the following table:

Cumulative Incidence Rate, %: Rifabutin (n=223)
Month | MAC Free and Alive | MAC | Adverse Experience | Lost to Follow-up
6 | 83.4 | 7.2 | 8.1 | 1.3
12 | 60.1 | 15.2 | 16.1 | 8.5
18 | 40.8 | 21.5 | 24.2 | 13.5
Cumulative Incidence Rate, %: Azithromycin (n=223)
Month | MAC Free and Alive | MAC | Adverse Experience | Lost to Follow-up
6 | 85.2 | 3.6 | 5.8 | 5.4
12 | 65.5 | 7.6 | 16.1 | 10.8
18 | 45.3 | 12.1 | 23.8 | 18.8
Cumulative Incidence Rate, %: Azithromycin/Rifabutin Combination (n=218)
Month | MAC Free and Alive | MAC | Adverse Experience | Lost to Follow-up
6 | 89.4 | 1.8 | 5.5 | 3.2
12 | 71.6 | 2.8 | 15.1 | 10.6
18 | 49.1 | 6.4 | 29.4 | 15.1

Comparing the cumulative one-year incidence rates, azithromycin monotherapy is at least as effective as rifabutin monotherapy. The difference (rifabutin – azithromycin) in the one-year rates (7.6%) is statistically significant (p=0.022) with an adjusted 95% confidence interval (0.9%, 14.3%). Additionally, azithromycin/rifabutin combination therapy is more effective than rifabutin alone. The difference (rifabutin – azithromycin/rifabutin) in the cumulative one-year incidence rates (12.5%) is statistically significant (p<0.001) with an adjusted 95% confidence interval of 6.6%, 18.4%. The comparable number of patients experiencing adverse events and the fewer number of patients lost to follow-up on rifabutin should be taken into account when interpreting the significance of this difference.

In Study 174, sensitivity testing^1 was performed on all available MAC isolates from subjects randomized to either azithromycin, rifabutin, or the combination. The distribution of MIC values for azithromycin from susceptibility testing of the breakthrough isolates was similar between trial arms. As the efficacy of azithromycin in the treatment of disseminated MAC has not been established, the clinical relevance of these in vitro MICs as an indicator of susceptibility or resistance is not known.

Clinically Significant Disseminated MAC Disease

In association with the decreased incidence of bacteremia, patients in the groups randomized to either azithromycin alone or azithromycin in combination with rifabutin showed reductions in the signs and symptoms of disseminated MAC disease, including fever or night sweats, weight loss, and anemia.

Discontinuations from Therapy for Drug-Related Side Effects

In Study 155, discontinuations for drug-related toxicity occurred in 8.2% of subjects treated with azithromycin and 2.3% of those given placebo (p=0.121). In Study 174, more subjects discontinued from the combination of azithromycin and rifabutin (22.7%) than from azithromycin alone (13.5%; p=0.026) or rifabutin alone (15.9%; p=0.209).

Safety

As these patients with advanced HIV disease were taking multiple concomitant medications and experienced a variety of intercurrent illnesses, it was often difficult to attribute adverse reactions to study medication. Overall, the nature of adverse reactions seen on the weekly dosage regimen of azithromycin over a period of approximately one year in patients with advanced HIV disease were similar to that previously reported for shorter course therapies.

INCIDENCE OF ONE OR MORE TREATMENT-RELATED [Includes those reactions considered possibly or probably related to study drug] ADVERSE REACTIONS [>2% adverse reaction rates for any group (except uveitis)] IN HIV INFECTED PATIENTS RECEIVING PROPHYLAXIS FOR DISSEMINATED MAC OVER APPROXIMATELY 1 YEAR
 | Study 155 |  | Study 174
 | Placebo | Azithromycin 1200 mg weekly | Azithromycin 1200 mg weekly | Rifabutin 300 mg daily | Azithromycin + Rifabutin
 | (N=91) | (N=89) | (N=233) | (N=236) | (N=224)
Mean Duration of Therapy (days) | 303.8 | 402.9 | 315 | 296.1 | 344.4
Discontinuation of Therapy | 2.3 | 8.2 | 13.5 | 15.9 | 22.7
Autonomic Nervous System
Mouth Dry | 0 | 0 | 0 | 3.0 | 2.7
Central Nervous System
Dizziness | 0 | 1.1 | 3.9 | 1.7 | 0.4
Headache | 0 | 0 | 3.0 | 5.5 | 4.5
Gastrointestinal
Diarrhea | 15.4 | 52.8 | 50.2 | 19.1 | 50.9
Loose Stools | 6.6 | 19.1 | 12.9 | 3.0 | 9.4
Abdominal Pain | 6.6 | 27 | 32.2 | 12.3 | 31.7
Dyspepsia | 1.1 | 9 | 4.7 | 1.7 | 1.8
Flatulence | 4.4 | 9 | 10.7 | 5.1 | 5.8
Nausea | 11 | 32.6 | 27.0 | 16.5 | 28.1
Vomiting | 1.1 | 6.7 | 9.0 | 3.8 | 5.8
General
Fever | 1.1 | 0 | 2.1 | 4.2 | 4.9
Fatigue | 0 | 2.2 | 3.9 | 2.1 | 3.1
Malaise | 0 | 1.1 | 0.4 | 0 | 2.2
Musculoskeletal
Arthralgia | 0 | 0 | 3.0 | 4.2 | 7.1
Psychiatric
Anorexia | 1.1 | 0 | 2.1 | 2.1 | 3.1
Skin & Appendages
Pruritus | 3.3 | 0 | 3.9 | 3.4 | 7.6
Rash | 3.2 | 3.4 | 8.1 | 9.4 | 11.1
Skin discoloration | 0 | 0 | 0 | 2.1 | 2.2
Special Senses
Tinnitus | 4.4 | 3.4 | 0.9 | 1.3 | 0.9
Hearing Decreased | 2.2 | 1.1 | 0.9 | 0.4 | 0
Uveitis | 0 | 0 | 0.4 | 1.3 | 1.8
Taste Perversion | 0 | 0 | 1.3 | 2.5 | 1.3

Adverse reactions related to the gastrointestinal tract were seen more frequently in patients receiving azithromycin than in those receiving placebo or rifabutin. In Study 174, 86% of diarrheal episodes were mild to moderate in nature with discontinuation of therapy for this reason occurring in only 9/233 (3.8%) of patients.

Changes in Laboratory Values

In these immunocompromised patients with advanced HIV infection, it was necessary to assess laboratory abnormalities developing on trial with additional criteria if baseline values were outside the relevant normal range.

PROPHYLAXIS AGAINST DISSEMINATED MAC ABNORMAL LABORATORY VALUES [excludes subjects outside of the relevant normal range at baseline]
 |  | Placebo |  | Azithromycin 1200 mg weekly |  | Rifabutin 300 mg daily |  | Azithromycin & Rifabutin
Hemoglobin | <8 g/dL | 1/51 | 2% | 4/170 | 2% | 4/114 | 4% | 8/107 | 8%
Platelet Count | <50 × 10^3/mm^3 | 1/71 | 1% | 4/260 | 2% | 2/182 | 1% | 6/181 | 3%
WBC Count | <1 × 10^3/mm^3 | 0/8 | 0% | 2/70 | 3% | 2/47 | 4% | 0/43 | 0%
Neutrophils | <500/mm^3 | 0/26 | 0% | 4/106 | 4% | 3/82 | 4% | 2/78 | 3%
SGOT | >5 × ULN [Upper Limit of Normal] | 1/41 | 2% | 8/158 | 5% | 3/121 | 3% | 6/114 | 5%
SGPT | >5 × ULN | 0/49 | 0% | 8/166 | 5% | 3/130 | 2% | 5/117 | 4%
Alk Phos | >5 × ULN | 1/80 | 1% | 4/247 | 2% | 2/172 | 1% | 3/164 | 2%

Treatment of Disseminated MAC Disease

One randomized, double-blind clinical trial (Study 189) was performed in patients with disseminated MAC. In this trial, 246 HIV-infected patients with disseminated MAC received either azithromycin 250 mg daily (N=65), azithromycin 600 mg daily (N=91), or clarithromycin 500 mg twice a day (N=90), each administered with ethambutol 15 mg/kg daily, for 24 weeks. Blood cultures and clinical assessments were performed every 3 weeks through week 12 and monthly thereafter through week 24. After week 24, patients were switched to any open-label therapy at the discretion of the investigator and followed every 3 months through the last follow-up visit of the trial. Patients were followed from the baseline visit for a period of up to 3.7 years (median: 9 months). MAC isolates recovered during treatment or post-treatment were obtained whenever possible.

The primary endpoint was sterilization by week 24. Sterilization was based on data from the central laboratory, and was defined as two consecutive observed negative blood cultures for MAC, independent of missing culture data between the two negative observations. Analyses were performed on all randomized patients who had a positive baseline culture for MAC.

The azithromycin 250 mg arm was discontinued after an interim analysis at 12 weeks showed a significantly lower clearance of bacteremia compared to clarithromycin 500 mg twice a day. Efficacy results for the azithromycin 600 mg daily and clarithromycin 500 mg twice a day treatment regimens are described in the following table:

RESPONSE TO THERAPY OF PATIENTS TAKING ETHAMBUTOL AND EITHER AZITHROMYCIN 600 MG DAILY OR CLARITHROMYCIN 500 MG TWICE A DAY
 | Azithromycin 600 mg daily | Clarithromycin 500 mg twice a day | [[95% confidence interval] on difference in rates (azithromycin-clarithromycin)] 95.1% CI on difference
Patients with positive culture at baseline | 68 | 57
Week 24
Two consecutive negative blood cultures [Primary endpoint] | 31/68 (46%) | 32/57 (56%) | [-28, 7]
Mortality | 16/68 (24%) | 15/57 (26%) | [-18, 13]

The primary endpoint, rate of sterilization of blood cultures (two consecutive negative cultures) at 24 weeks, was lower in the azithromycin 600 mg daily group than in the clarithromycin 500 mg twice a day group.

Sterilization by Baseline Colony Count

Within both treatment groups, the sterilization rates at week 24 decreased as the range of MAC cfu/mL increased.

 | Azithromycin 600 mg (N=68) | Clarithromycin 500 mg twice a day (N=57)
groups stratified by MAC colony counts at baseline | no. (%) subjects in stratified group sterile at week 24 | no. (%) subjects in stratified group sterile at week 24
≤10 cfu/mL | 10/15 (66.7%) | 12/17 (70.6%)
11–100 cfu/mL | 13/28 (46.4%) | 13/19 (68.4%)
101–1,000 cfu/mL | 7/19 (36.8%) | 5/13 (38.5%)
1,001–10,000 cfu/mL | 1/5 (20.0%) | 1/5 (20%)
>10,000 cfu/mL | 0/1 (0.0%) | 1/3 (33.3%)

Susceptibility Pattern of MAC Isolates

Susceptibility testing was performed on MAC isolates recovered at baseline, at the time of breakthrough on therapy or during post-therapy follow-up. The T100 radiometric broth method was employed to determine azithromycin and clarithromycin MIC values. Azithromycin MIC values ranged from <4 to >256 µg/mL and clarithromycin MICs ranged from <1 to >32 µg/mL. The individual MAC susceptibility results demonstrated that azithromycin MIC values could be 4 to 32-fold higher than clarithromycin MIC values.

During treatment and post-treatment follow-up for up to 3.7 years (median: 9 months) in Study 189, a total of 6/68 (9%) and 6/57 (11%) of the patients randomized to azithromycin 600 mg daily and clarithromycin 500 mg twice a day respectively, developed MAC blood culture isolates that had a sharp increase in MIC values. All twelve MAC isolates had azithromycin MICs ≥256 µg/mL and clarithromycin MICs >32 µg/mL. These high MIC values suggest development of drug resistance. However, at this time, specific breakpoints for separating susceptible and resistant MAC isolates have not been established for either macrolide.

15 REFERENCES

1. Griffith DE, Aksamit T, Brown-Elliot BA, et al. An official ATS/IDSA statement: Diagnosis, treatment, and prevention of nontuberculous mycobacterial diseases. Am J Respir Crit Care Med. 2007; 175:367–416.

16 HOW SUPPLIED/STORAGE AND HANDLING

ZITHROMAX 600 mg tablets (engraved on front with "PFIZER" and on back with "308") are supplied as white, modified oval-shaped, film-coated tablets containing azithromycin dihydrate equivalent to 600 mg azithromycin. These are packaged in bottles of 30 tablets. ZITHROMAX tablets are supplied as follows:

Bottles of 30 | NDC 0069-3080-30

Tablets should be stored at or below 30°C (86°F).

ZITHROMAX for oral suspension is supplied in single-dose packets containing azithromycin dihydrate equivalent to 1 gram of azithromycin as follows:

Boxes of 3 single-dose packets (1 g) | NDC 0069-3051-75

STORAGE AND HANDLING

Store single-dose packets below 30°C (86°F).

17 PATIENT COUNSELING INFORMATION

ZITHROMAX tablets may be taken with or without food. However, increased tolerability has been observed when tablets are taken with food.

ZITHROMAX for oral suspension in single 1 g packets can be taken with or without food after constitution.

Patients should also be cautioned not to take aluminum- and magnesium-containing antacids and azithromycin simultaneously.

The patient should be directed to discontinue azithromycin immediately and contact a physician if any signs of an allergic reaction occur.

Direct parents or caregivers to contact their physician if vomiting and irritability with feeding occurs in the infant.

Patients should be counseled that antibacterial drugs, including ZITHROMAX, should only be used to treat bacterial infections. They do not treat viral infections (e.g., the common cold). When ZITHROMAX is prescribed to treat bacterial infection, patients should be told that although it is common to feel better early in the course of therapy, the medication should be taken exactly as directed. Skipping doses or not completing the full course of therapy may (1) decrease the effectiveness of the immediate treatment and (2) increase the likelihood that bacteria will develop resistance and will not be treatable by ZITHROMAX or other antibacterial drugs in the future.

Diarrhea is a common problem caused by antibacterial which usually ends when the antibiotic is discontinued. Sometimes after starting treatment with antibacterials, patients can develop watery and bloody stools (with or without stomach cramps and fever) even as late as two or more months after having taken the last dose of the antibacterial. If this occurs, patients should contact their physician as soon as possible.

Licensed from Pliva

This product's label may have been updated. For current full prescribing information, please visit www.pfizer.com.

LAB-0022-23.0

PRINCIPAL DISPLAY PANEL - 600 mg Tablet Bottle Label

NDC 0069-3080-30

Pfizer

Zithromax®
(azithromycin) tablets
600 mg*

30 Tablets
Rx only

PRINCIPAL DISPLAY PANEL - 1 g Packet Label

Pfizer
NDC 0069-3051-01

Zithromax®
(azithromycin)
for oral suspension

1 g*

FOR ORAL ADMINISTRATION

Single Dose Packet
Rx only

PRINCIPAL DISPLAY PANEL - 1 g Packet Box

Pfizer
NDC 0069-3051-75

Zithromax®
(azithromycin)
for oral suspension

1 g*

FOR ORAL ADMINISTRATION

3 Single Dose Packets
Rx only